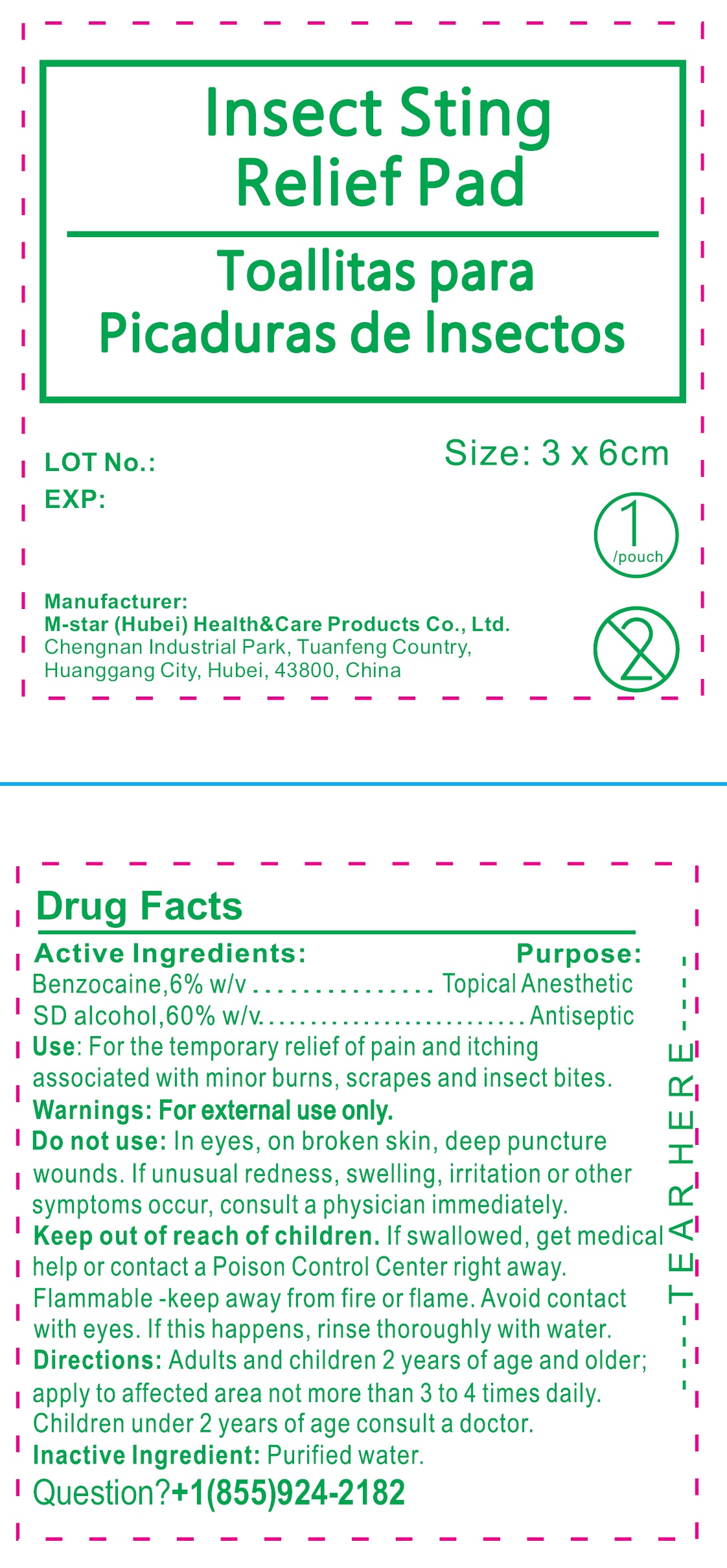 DRUG LABEL: Insect Sting Relief Pad TOALLITAS PARA PICADURAS DE INSECTOS
NDC: 84219-003 | Form: CLOTH
Manufacturer: M-star (Hubei) Health&Care Products Co., Ltd.
Category: otc | Type: HUMAN OTC DRUG LABEL
Date: 20240401

ACTIVE INGREDIENTS: BENZOCAINE 6 g/100 g; ALCOHOL 60 g/100 g
INACTIVE INGREDIENTS: WATER

Insect Sting Relief Pad TOALLITAS PARA PICADURAS DE INSECTOS

Active ingredient:

Benzocaine, 6% w/v

SD alcohol, 60% w/v

Purpose:

Topical Anesthetic

Antiseptic

Use:

For the temporary relief of pain and itching associated with minor burns, scrapes and insect bites.

Warnings:

For external use only.

Do not use:

In eyes, on broken skin, deep puncture wounds. If unusual redness, swelling, irritation or other symptoms occur, consult a physician immediately.

Keep out of reach of children.

If swallowed, get medical help or contact a Poison Control Center right away.

Flammable -keep away from fire or flame. Avoid contact with eyes. If this happens, rinse thoroughly with water.

Directions:

Adults and children 2 years of age and older; apply to affected area not more than 3 to 4 times daily. Children under 2 years of age consult a doctor.

Inactive ingredient:

Purified water.

Question?

+1(855)924-2182